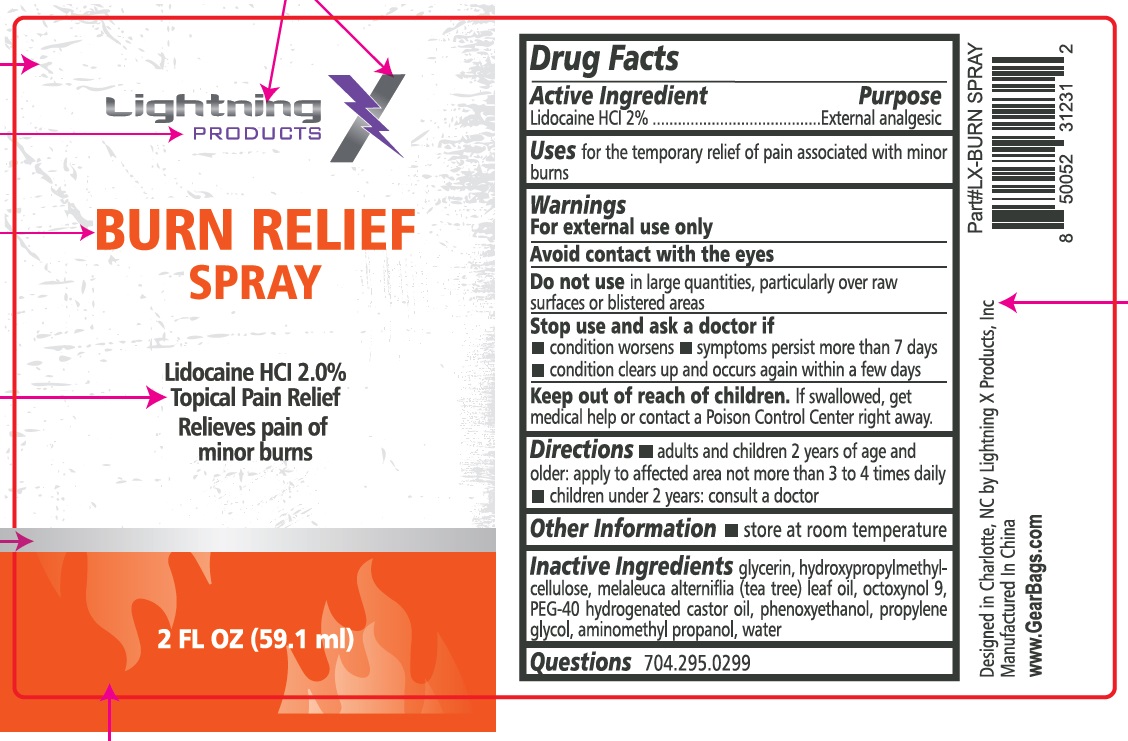 DRUG LABEL: Lightning Products BURN RELIEF
NDC: 43473-070 | Form: SPRAY
Manufacturer: Nantong Health & Beyond Hygienic Products Inc.
Category: otc | Type: HUMAN OTC DRUG LABEL
Date: 20250227

ACTIVE INGREDIENTS: LIDOCAINE HYDROCHLORIDE 2 g/100 mL
INACTIVE INGREDIENTS: WATER; HYDROXYPROPYL METHYLCELLULOSE; MELALEUCA ALTERNIFOLIA (TEA TREE) LEAF OIL; OCTOXYNOL 9; PEG-40 HYDROGENATED CASTOR OIL; GLYCERIN; PHENOXYETHANOL; PROPYLENE GLYCOL; AMINOMETHYL PROPANOL

43473-070 Ligthning Products Burn Spray

Active ingredient

Lidocaine HCI 2%

Purpose

External Analgesic

Uses

For temporary relief of pain associated with minor burns.

Warnings

For external use only.

Avoid contact with eyes

Do not use

■ in large quantities, particularly over raw surface or blistered areas

Stop use and ask a doctor

- if the condition worsens
- symptoms persist for more than 7 days
- condition clears up and occurs again within a few days

Keep out of reach of children. If swallowed, get medical help or contact a Poison Control Center right away

Directions

Adults and children 2 years of age or older:apply to affected area not more than 3 to 4 times daily

Chilrdren under 2 years old: consult a doctor

Inactive ingredients

glycerin, Hydroxypropyl methylcellulose, melaleuca alterniflia (tea tree) leaf oil, octoxyol 9, PEG-40 hydrogenated castor oil, Phenoxyethanol, Polyethylene Glycol, Aminomethyl Propanol, Water